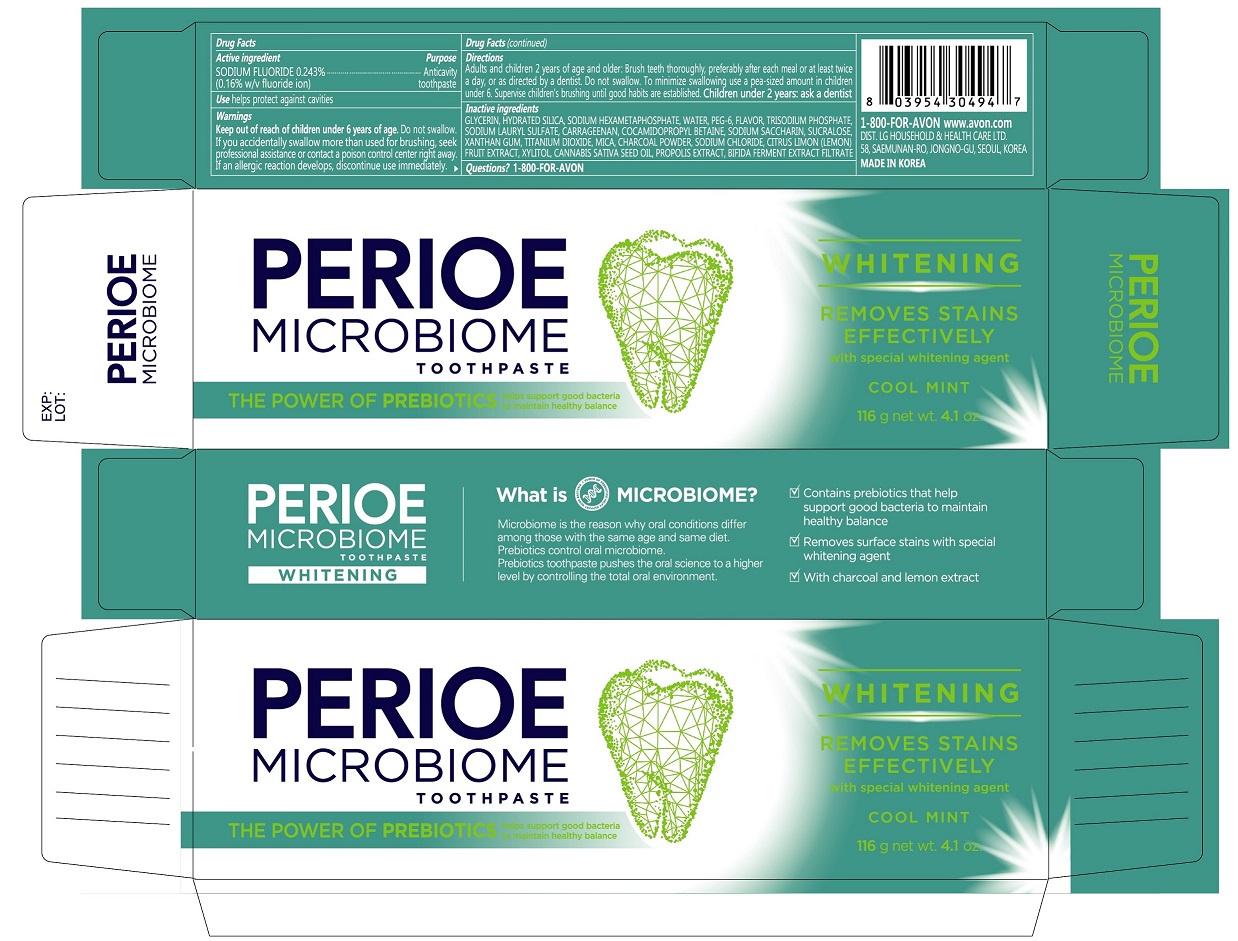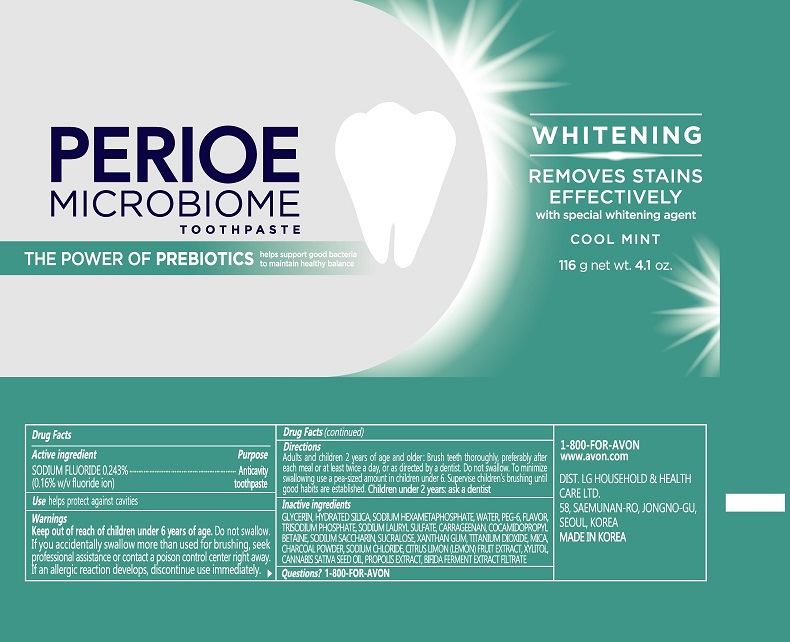 DRUG LABEL: PERIOE Microbiome Whitening
NDC: 43136-810 | Form: PASTE, DENTIFRICE
Manufacturer: Tai Guk Pharm. Co., Ltd.
Category: otc | Type: HUMAN OTC DRUG LABEL
Date: 20250101

ACTIVE INGREDIENTS: SODIUM FLUORIDE 1.6 mg/1 g
INACTIVE INGREDIENTS: POLYETHYLENE GLYCOL 300; PROPOLIS WAX; SODIUM POLYMETAPHOSPHATE; CARRAGEENAN; GLYCERIN; WATER; COCAMIDOPROPYL BETAINE; SODIUM PHOSPHATE, TRIBASIC, ANHYDROUS; SODIUM LAURYL SULFATE; XYLITOL; SACCHARIN SODIUM; SUCRALOSE; TITANIUM DIOXIDE; CITRUS LIMON FRUIT OIL; SODIUM CHLORIDE; HYDRATED SILICA; XANTHAN GUM; MICA; ACTIVATED CHARCOAL; CANNABIS SATIVA SEED OIL

PERIOE Microbiome Whitening Toothpaste Cool Mint 116 g

Drug Facts

Active Ingredient

Sodium fluoride 0.243% (0.16% w/v fluoride ion)

Purpose

Anticavity toopaste

Use

helps protect against cavities

Warnings

Keep out of reach of children under 6 years of age.Do not swallow. If you accidentally swallow more than used for brushing, seek professional assistance or contact a poison control center right away. If an allergic reaction develops, discontinue use immediately.

Directions

Adults and children 2 years of age and and older: Brush teeth thoroughly, preferably after each meal or at least twice a day, or as directed by a dentist. Do not swallow. To minimize swallowing use a pea-sized amount in children under 6. Supervise children's brushing until good habits are established. Children under 2 years: ask a dentist.

Inactive Ingredients

GLYCERIN, HYDRATED SILICA, SODIUM HEXAMETAPHOSPHATE, WATER, PEG-6, FLAVOR, TRISODIUM PHOSPHATE, SODIUM LAURYL SULFATE, CARRAGEENAN, COCAMIDOPROPYL BETAINE, SODIUM SACCHARIN, SUCRALOSE, XANTHAN GUM, TITANIUM DIOXIDE, MICA, CHARCOAL POWDER, SODIUM CHLORIDE, CITRUS LIMON(LEMON) FRUIT EXTRACT, XYLITOL, CANNABIS SATINA SEED OIL, PROPOLIS EXTRACT, BIFIDA FERMENT EXTRACT FILTRATE

Questions?

1-800-FOR-AVON

Principal Display Panel - 116 g Tube Carton

PERIOE
MICROBIOME
TOOTHPASTE

THE POWER OF PREBIOTICS
helps support good bacteria
to maintain healthy balance

WHITENING

REMOVES STAINS EFFECTIVELY
with special whitening agent
COOL MINT

116 g net wt. 4.1. oz